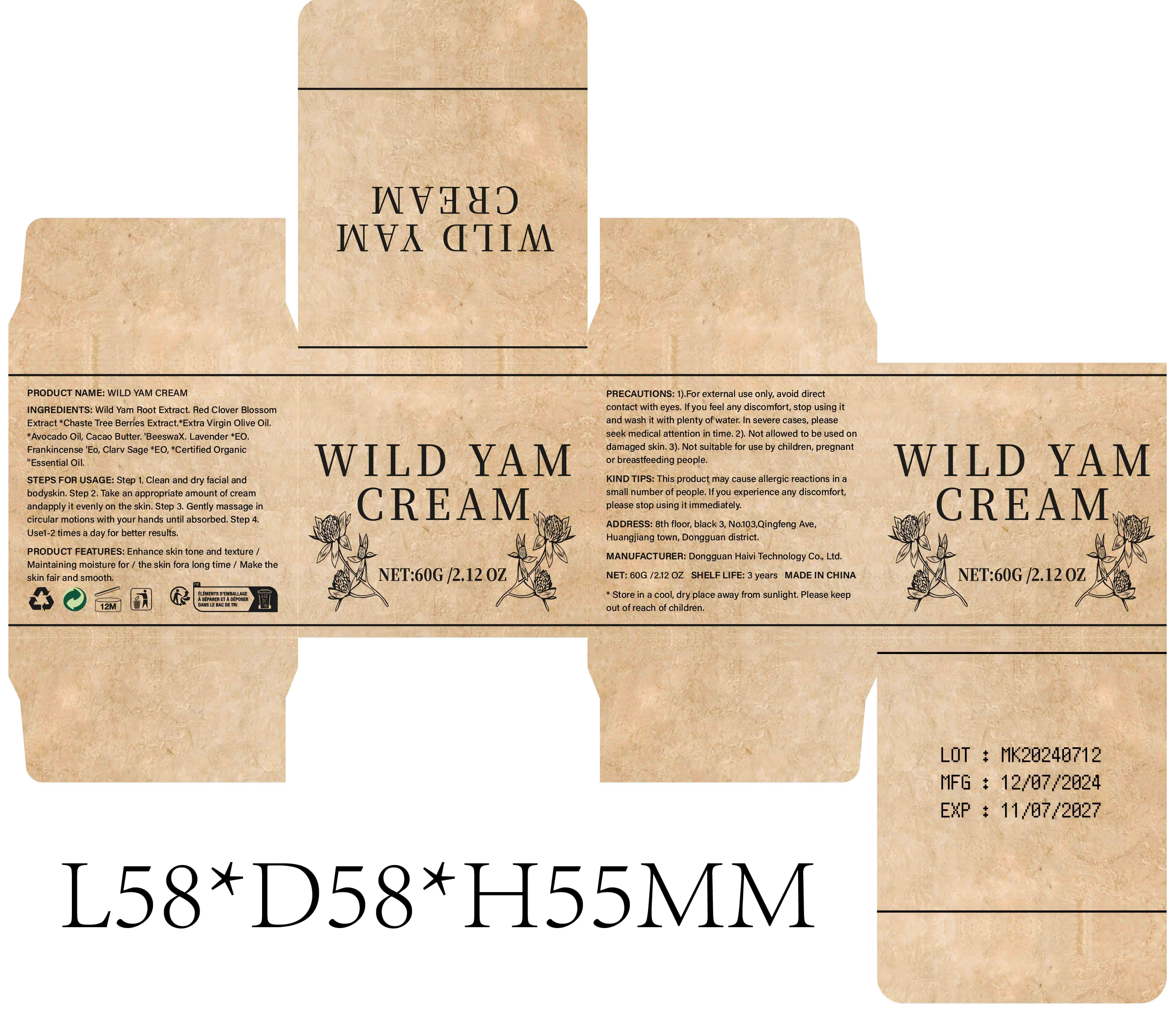 DRUG LABEL: WILD YAM Cream
NDC: 84732-043 | Form: CREAM
Manufacturer: Dongguan Haiyi Technology Co.,Ltd.
Category: otc | Type: HUMAN OTC DRUG LABEL
Date: 20241014

ACTIVE INGREDIENTS: DIOSCOREA VILLOSA TUBER 1 mg/100 g
INACTIVE INGREDIENTS: PEG-8 BEESWAX; LAVENDER OIL; FRANKINCENSE; TRIFOLIUM PRATENSE FLOWER; OLIVE OIL; THEOBROMA CACAO WHOLE; AVOCADO OIL; VITEX AGNUS-CASTUS WHOLE

Active ingredient

Wild Yam Root Extract

Inactive ingredient

Red Clover BlossomExtract *Chaste Tree Berries Extract.*Extra Virgin Olive Oil.*Avocado Oil, Cacao Butter.'BeeswaX. Lavender *EO.Frankincense 'Eo, Clarv Sage *EO, *Certified Organic"Essential Oil.

Purpose section

Enhance skin tone and texture

Maintaining moisture for

the skin fora long time

Make theskin fair and smooth.

Warning

1).For external use only, avoid directcontact with eyes, lf you feel any discomfort, stop using itand wash it with plenty of water, In severe cases, pleaseseek medical attention in time.

2). Not allowed to be used ondamaged skin.

3). Not suitable for use by children, pregnantor breastfeeding people.

stop use

This product may cause allergic reactions in asmall number of people.

lf you experience any discomfort,please stop using it immediately.

not use

This product may cause allergic reactions in asmall number of people.

OUT OF CHILDREN

KEEP THE PRODUCT OUT OF REACH OF CHILDREN to

HOW TO USE

Step 1. Clean and dry facial andbodyskin.

Step 2. Take an appropriate amount of creamandapply it evenly on the skin.

Step 3. Gently massage incircular motions with your hands until absorbed.

Step 4.Use1-2 times a day for better results.

Dosage

Use1-2 times a day for better results.